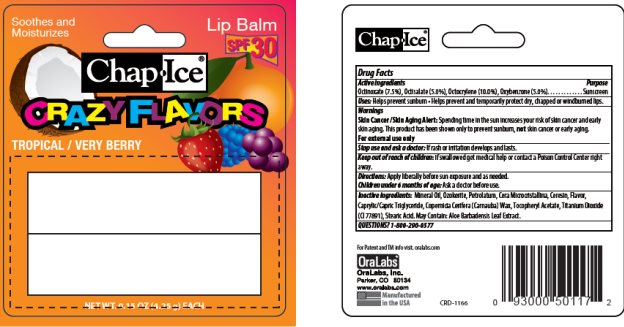 DRUG LABEL: ChapIce SPF 30 Lip Balm
NDC: 63645-163 | Form: STICK
Manufacturer: OraLabs
Category: otc | Type: HUMAN OTC DRUG LABEL
Date: 20250507

ACTIVE INGREDIENTS: OCTINOXATE 7.5 mg/1 g; OXYBENZONE 5 mg/1 g; OCTOCRYLENE 10 mg/1 g; OCTISALATE 5 mg/1 g
INACTIVE INGREDIENTS: PETROLATUM 13 mg/1 g; LIGHT MINERAL OIL 25.5 mg/1 g; .ALPHA.-TOCOPHEROL ACETATE 0.1 mg/1 g; CERESIN 36 mg/1 g; MICROCRYSTALLINE WAX 4 mg/1 g

Drug Facts

Active ingredient

Octinoxate (7.5%), Octocrylene (10.0%), Oxybenzone (5.0%), Octisalate (5.0%)

Purpose

Sunscreen, Sunscreen, Sunscreen, Sunscreen

Keep Out of Reach of Children

If swallowed get medical help or contact a Poison Control Center right away.

Uses

Prevents Sunburns

Warnings

Skin Cancer/Skin Aging Alert: Spending time in the sun increases your risk of skin cancer and early skin aging. This product has been shown only to prevent sunburn, not skin cancer or early aging.

For external use only: Stop use and ask a doctor: if rash or irritation develops and lasts.

Directions

Apply liberally before sun exposure and as needed. Children under 6 months of age: Ask a doctor before use.

Inactive Ingredients

Mineral Oil, Ozokerite, Petrolatum, Microcrystalline Wax, Ceresin, Flavor, Copernicia Cerifera (Carnauba) Wax, Caprylic/Capric Triglyceride, Titanium Dioxide (CI 77891), Stearic Acid, Tocopheryl Acetate, Aluminum Hydroxide.